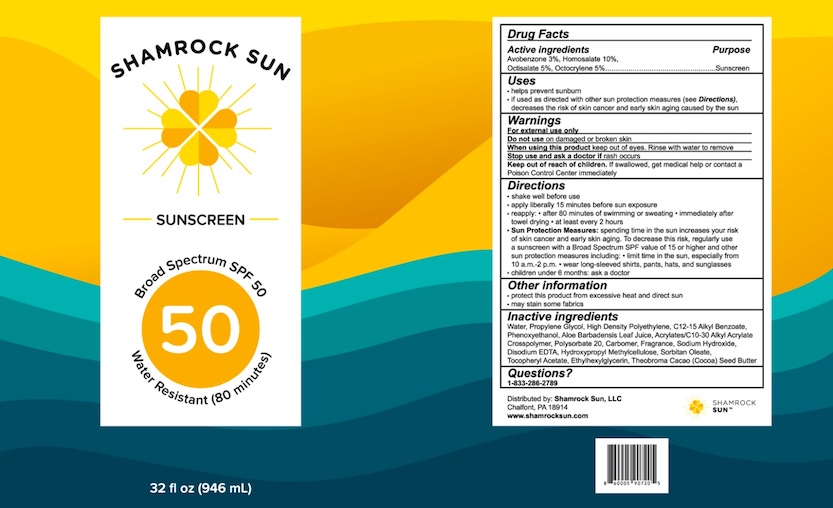 DRUG LABEL: Shamrock Sun SPF50
NDC: 80975-001 | Form: LOTION
Manufacturer: Shamrock Sun, LLC
Category: otc | Type: HUMAN OTC DRUG LABEL
Date: 20210125

ACTIVE INGREDIENTS: OCTISALATE 5 g/100 mL; OCTOCRYLENE 5 g/100 mL; HOMOSALATE 10 g/100 mL; AVOBENZONE 3 g/100 mL
INACTIVE INGREDIENTS: CARBOMER HOMOPOLYMER, UNSPECIFIED TYPE; SORBITAN MONOOLEATE; .ALPHA.-TOCOPHEROL ACETATE; POLYSORBATE 20; HIGH DENSITY POLYETHYLENE; ALKYL (C12-15) BENZOATE; PROPYLENE GLYCOL; PHENOXYETHANOL; ETHYLHEXYLGLYCERIN; COCOA BUTTER; HYPROMELLOSE, UNSPECIFIED; CARBOMER COPOLYMER TYPE A (ALLYL PENTAERYTHRITOL CROSSLINKED); ALOE VERA LEAF; WATER; EDETATE DISODIUM; SODIUM HYDROXIDE

SHAMROCK SUN SPF 50 SUNSCREEN

Drug Facts

Active ingredients

Avobenzone 3%, Homosalate 10%, Octislate 5%, Octocrylene 5%

Purpose

Sunscreen

Uses

- helps prevent sunburn
- if used as directed with other sun protection measures (see Directions), decreases the risk of skin cancer and early skin aging caused by the sun.

Warnings

For external use only

Do not use on damaged or broken skin

When using this product keep out of eyes. Rinse with water to remove

Stop use and ask doctor if rash occurs

Keep out of reach of children. If swallowed, get medical help or contact a Poison Control Center immediately.

Directions:

- shake well before use
- apply liberally 15 minutes before sun exposure
- reapply:
- after 80 minutes of swimming or sweating
- immediately after towel drying
- at least every 2 hours
- Sun Protection Measures. Spending time in the sun increases your risk of skin cancer and early skin aging. To decrease this risk, regularly use a sunscreen with a Broad Spectrum SPF value of 15 or higher and other sun protection measures including
- limit time in the sun, especially from 10 a.m. - 2 p.m.
- wear long-sleeved shirts, pants, hats and sunglasses.
- children under 6 months: ask a doctor.

Other information

- protect this product from excessive heat and direct sun
- may stain some fabrics

INACTIVE INGREDIENT

Inactive ingredients Water, Propylene Glycol, High Density Polyethylene, C12-15 Alkyl Benzoate, Phenoxyethanol, Aloe Barbadensis Leaf Juice, Acrylates/C10-30 Alkyl Acrylate Crosspolymer, Polysorbate 20, Carbomer, Fragrance, Sodium Hydroxide, Disodium EDTA, Hydroxypropyl Methylcellulose, Sorbitan Oleate, Tocopheryl Acetate, Ethylhexylglycerin, Theobroma Cacao (Cocoa) Seed Butter

Questions?

1-833-286-2789

Distributed by: Shamrock Sun, LLC

Chalfont, PA 18914

www.shamrocksun.com

PACKAGE LABEL

SHAMROCK SUN

SUNSCREEN

Broad Spectrum SPF 50

50

Water Resistant (80 Minutes)

32 fl oz (946 mL)